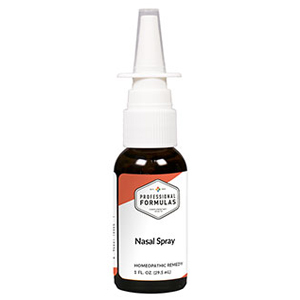 DRUG LABEL: Allergy Liquescence
NDC: 63083-3031 | Form: LIQUID
Manufacturer: Professional Complementary Health Formulas
Category: homeopathic | Type: HUMAN OTC DRUG LABEL
Date: 20190815

ACTIVE INGREDIENTS: ONION 1 [hp_X]/118 mL; AMBROSIA TENUIFOLIA WHOLE 1 [hp_X]/118 mL; APIS MELLIFERA 1 [hp_X]/118 mL; EUPHRASIA STRICTA 1 [hp_X]/118 mL; ECHINACEA ANGUSTIFOLIA WHOLE 2 [hp_X]/118 mL; EPHEDRA DISTACHYA FLOWERING TWIG 3 [hp_X]/118 mL; SCHOENOCAULON OFFICINALE SEED 3 [hp_X]/118 mL; SUS SCROFA ADRENAL GLAND 6 [hp_X]/118 mL; EPINEPHRINE 6 [hp_X]/118 mL; GALIUM APARINE WHOLE 6 [hp_X]/118 mL; GOLDENSEAL 6 [hp_X]/118 mL; BEEF LIVER 6 [hp_X]/118 mL; HISTAMINE DIHYDROCHLORIDE 12 [hp_X]/118 mL
INACTIVE INGREDIENTS: ALCOHOL; WATER

T31

ACTIVE INGREDIENTS

Allium cepa 1X
Ambrosia 1X
Apis mellifica 1X
Euphrasia officinalis 1X
Echinacea angustifolia 2X
Ephedra 3X
Sabadilla 3X
Adrenal 6X
Adrenalinum 6X
Galium aparine 6X
Hydrastis canadensis 6X
Liver 6X
Histaminum hydrochloricum 12X

QUESTIONS

Professional Formulas

PO Box 2034 Lake Oswego, OR 97035

INDICATIONS

For the temporary relief of sneezing, runny nose, nasal congestion, red, watery, and itchy eyes, coughing, fatigue, or occasional headache.*

PURPOSE

*Claims based on traditional homeopathic practice, not accepted medical evidence. Not FDA evaluated.

WARNINGS

In case of overdose, get medical help or contact a poison control center right away.

Keep out of the reach of children.

PREGNANCY OR BREAST FEEDING

If pregnant or breastfeeding, ask a healthcare professional before use.

DIRECTIONS

Place drops under tongue 30 minutes before/after meals. Adults and children 12 years and over: Take one full dropper up to 2 times per day. For immediate onset of symptoms, take 10 to 15 drops every 15 minutes up to 3 hours. For less severe symptoms, take 10-15 drops hourly up to 8 hours. Consult a physician for use in children under 12 years of age.

OTHER INFORMATION

Tamper resistant. If seal is broken, do not use. After opening, close container tightly and store at room temperature away from heat.

INACTIVE INGREDIENTS

20% ethanol, purified water.

LABEL

Est 1985

Professional Formulas

Complementary Health

Allergy Liquescence

Homeopathic Remedy

4 FL. OZ. (118 mL)